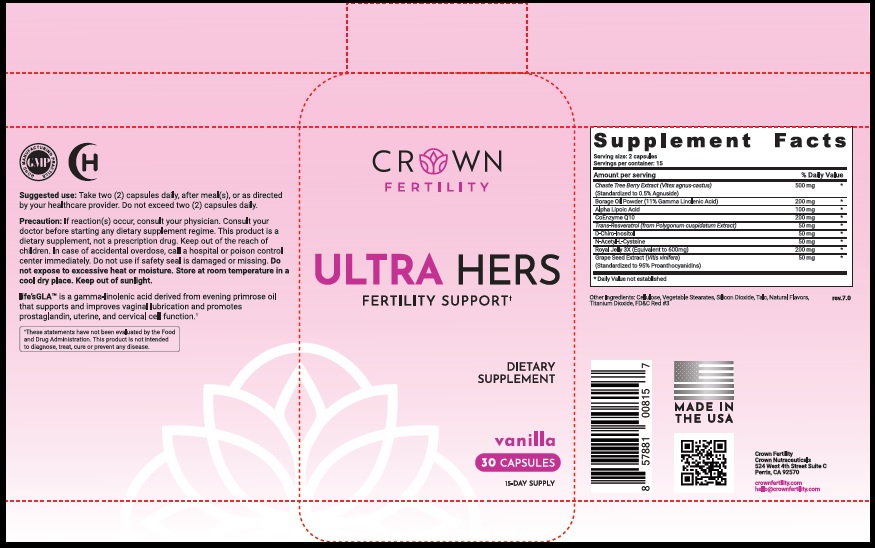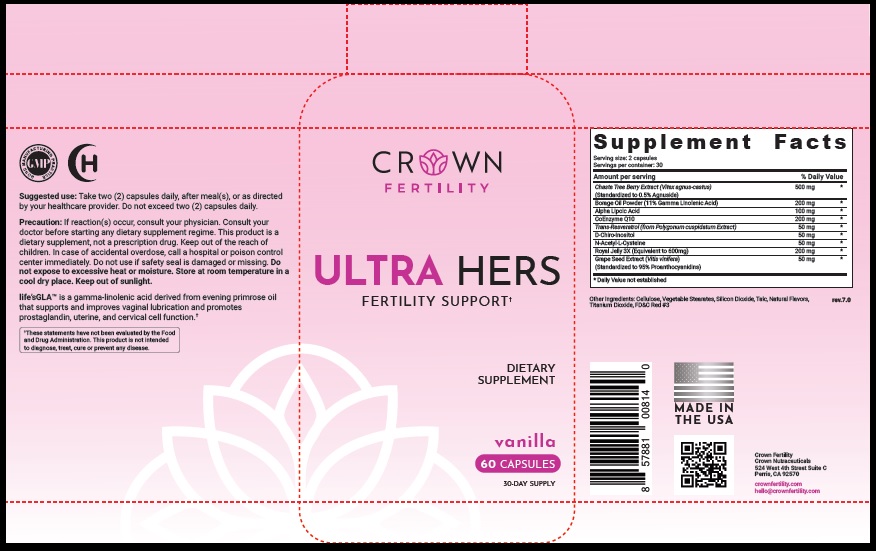 DRUG LABEL: ULTRA HERS VANILLA
NDC: 73489-004 | Form: CAPSULE
Manufacturer: CROWN GENERAL AGENCY INC
Category: other | Type: Dietary Supplement
Date: 20211021

ACTIVE INGREDIENTS: CHASTE TREE FRUIT 500 mg/1 1; GAMOLENIC ACID 200 mg/1 1; THIOCTIC ACID 100 mg/1 1; UBIDECARENONE 200 mg/1 1; REYNOUTRIA JAPONICA LEAF 50 mg/1 1; CHIRO-INOSITOL, (+)- 50 mg/1 1; ACETYLCYSTEINE 50 mg/1 1; ROYAL JELLY 200 mg/1 1; VITIS VINIFERA SEED 50 mg/1 1
INACTIVE INGREDIENTS: POWDERED CELLULOSE; MAGNESIUM STEARATE; SILICON DIOXIDE; TALC; TITANIUM DIOXIDE; FD&C RED NO. 3

STATEMENT OF IDENTITY

Dietary Supplement

Suggested Use

Take two (2) capsules daily, after meal(s), or as directed by your healthcare provider. Do not exceed two (2) capsules daily.

Precaution

If reaction(s) occur, consult your physician. Consult your doctor before starting any dietary supplement regime. This product is a dietary supplement, not a prescription drug. Keep out of the reach of children. In case of accidental overdose, call a hospital or poison control center immediately. Do not use if safety seal is damaged or missing. Do not expose to excessive heat or moisture. Store at room temperature in a cool dry place. Keep out of sunlight.